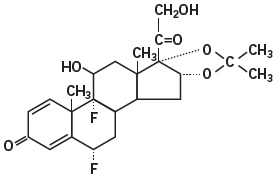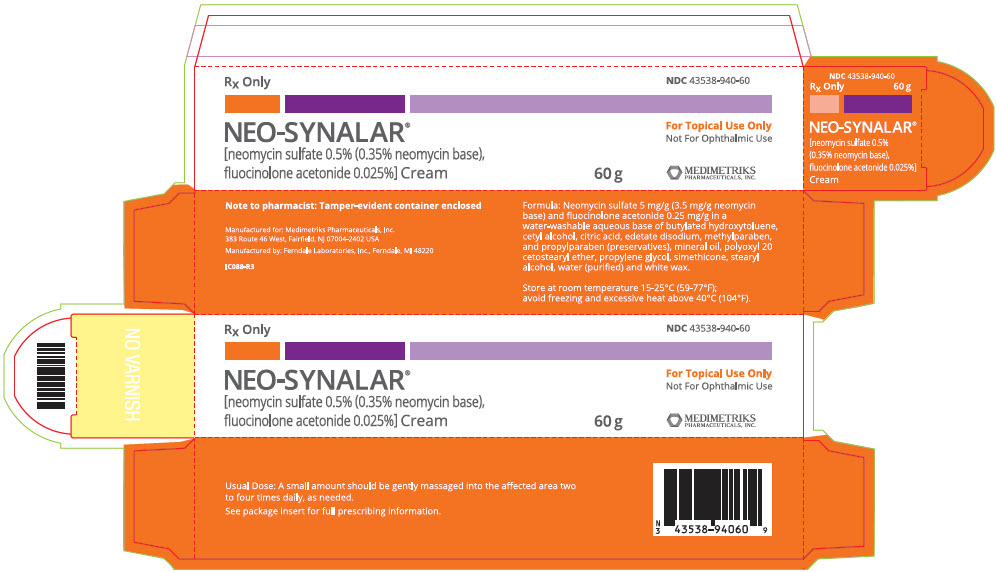 DRUG LABEL: Neo-Synalar
NDC: 43538-940 | Form: CREAM
Manufacturer: Medimetriks Pharmaceuticals
Category: prescription | Type: HUMAN PRESCRIPTION DRUG LABEL
Date: 20230110

ACTIVE INGREDIENTS: neomycin sulfate 3.5 mg/1 g; fluocinolone acetonide 0.25 mg/1 g
INACTIVE INGREDIENTS: butylated hydroxytoluene; cetyl alcohol; citric acid monohydrate; edetate disodium; propylparaben; methylparaben; mineral oil; polyoxyl 20 cetostearyl ether; propylene glycol; stearyl alcohol; water; white wax

NEO-SYNALAR®
[neomycin sulfate 0.5% (0.35% neomycin base), fluocinolone acetonide 0.025%] Cream

Rx Only

DESCRIPTION

NEO-SYNALAR® cream is intended for topical administration. The active component is the corticosteroid fluocinolone acetonide, which has the chemical name pregna-1,4-diene-3,20-dione,6,9-difluoro-11,21-dihydroxy-16,17-[(1-methylethylidene)bis (oxy)]-,(6α,11β,16α)-, and the antibacterial neomycin sulfate. Fluocinolone acetonide has the following chemical structure:

The cream contains neomycin sulfate 5 mg/g (3.5 mg/g neomycin base) and fluocinolone acetonide 0.25 mg/g in a water-washable aqueous base of butylated hydroxytoluene, cetyl alcohol, citric acid, edetate disodium, methylparaben and propylparaben (preservatives), mineral oil, polyoxyl 20 cetostearyl ether, propylene glycol, simethicone, stearyl alcohol, water (purified) and white wax.

CLINICAL PHARMACOLOGY

Topical corticosteroids share anti-inflammatory, anti-pruritic and vasoconstrictive actions.

The mechanism of anti-inflammatory activity of the topical corticosteroids is unclear. Various laboratory methods, including vasoconstrictor assays, are used to compare and predict potencies and/or clinical efficacies of the topical corticosteroids. There is some evidence to suggest that a recognizable correlation exists between vasoconstrictor potency and therapeutic efficacy in man.

Pharmacokinetics

The extent of percutaneous absorption of topical corticosteroids is determined by many factors including the vehicle, the integrity of the epidermal barrier, and the use of occlusive dressings.

Topical corticosteroids can be absorbed from normal intact skin. Inflammation and/or other disease processes in the skin increase percutaneous absorption. Occlusive dressings substantially increase the percutaneous absorption of topical corticosteroids.

Once absorbed through the skin, topical corticosteroids are handled through pharmacokinetic pathways similar to systemically administered corticosteroids. Corticosteroids are bound to plasma proteins in varying degrees. Corticosteroids are metabolized primarily in the liver and are then excreted by the kidneys. Some of the topical corticosteroids and their metabolites are also excreted into the bile.

INDICATIONS AND USAGE

NEO-SYNALAR® cream is indicated for the treatment of corticosteroid-responsive dermatoses with secondary infection. It has not been demonstrated that this steroid-antibiotic combination provides greater benefit than the steroid component alone after 7 days of treatment (see WARNINGS section).

CONTRAINDICATIONS

Topical corticosteroids are contraindicated in those patients with a history of hypersensitivity to any of the components of the preparation. This product should not be used in the external auditory canal if the eardrum is perforated.

WARNINGS

If local infection should continue or become severe, or in the presence of systemic infection, appropriate systemic antibacterial therapy, based on susceptibility testing, should be considered.

Because of the concern of nephrotoxicity and ototoxicity associated with neomycin, this combination product should not be used over a wide area or for extended periods of time.

There are articles in the current medical literature that indicate an increase in the prevalence of persons sensitive to neomycin.

PRECAUTIONS

General

It is recommended that NEO-SYNALAR® cream not be used under occlusive dressings. Systemic absorption of topical corticosteroids has produced reversible hypothalamic-pituitary-adrenal (HPA) axis suppression, manifestations of Cushing's syndrome, hyperglycemia, and glucosuria in some patients.

Conditions which augment systemic absorption include the application of the more potent steroids, use over large surface areas, prolonged use.

Therefore, patients receiving a large dose of a potent topical steroid applied to a large surface area should be evaluated periodically for evidence of HPA axis suppression by using the urinary free cortisol and ACTH stimulation tests. If HPA axis suppression is noted, an attempt should be made to withdraw the drug, to reduce the frequency of application, or to substitute a less potent steroid.

Recovery of HPA axis function is generally prompt and complete upon discontinuation of the drug. Infrequently, signs and symptoms of steroid withdrawal may occur, requiring supplemental systemic corticosteroids.

Children may absorb proportionally larger amounts of topical corticosteroids and thus be more susceptible to systemic toxicity (see PRECAUTIONS—Pediatric Use).

If irritation develops, topical corticosteroids should be discontinued and appropriate therapy instituted.

As with any topical corticosteroid product, prolonged use may produce atrophy of the skin and subcutaneous tissues. When used on intertriginous or flexor areas, or on the face, this may occur even with short-term use.

Information for the Patient

Patients using topical corticosteroids should receive the following information and instructions:

1. This medication is to be used as directed by the physician. It is for external use only. Avoid contact with the eyes.
2. Patients should be advised not to use this medication for any disorder other than that for which it was prescribed.
3. The treated skin area should not be bandaged or otherwise covered or wrapped as to be occlusive unless directed by the physician.
4. Patients should report any signs of local adverse reactions, especially under occlusive dressing.
5. Parents of pediatric patients should be advised not to use tight-fitting diapers or plastic pants on a child being treated in the diaper area, as these garments may constitute occlusive dressings.

Laboratory Tests

The following tests may be helpful in evaluating the HPA axis suppression:

Urinary free cortisol test
ACTH stimulation test

Carcinogenesis, Mutagenesis, and Impairment of Fertility

Long-term animal studies have not been performed to evaluate the carcinogenic potential or the effect on fertility of topical corticosteroids.

Studies to determine mutagenicity with prednisolone and hydrocortisone have revealed negative results.

Pregnancy Category C

Corticosteroids are generally teratogenic in laboratory animals when administered systemically at relatively low dosage levels. The more potent corticosteroids have been shown to be teratogenic after dermal application in laboratory animals. There are no adequate and well-controlled studies in pregnant women on teratogenic effects from topically applied corticosteroids. Therefore, topical corticosteroids should be used during pregnancy only if the potential benefit justifies the potential risk to the fetus. Drugs of this class should not be used extensively on pregnant patients, in large amounts, or for prolonged periods of time.

Nursing Mothers

It is not known whether topical administration of corticosteroids could result in sufficient systemic absorption to produce detectable quantities in breast milk. Systemically administered corticosteroids are secreted into breast milk in quantities not likely to have a deleterious effect on the infant. Nevertheless, caution should be exercised when topical corticosteroids are administered to a nursing woman.

Pediatric Use

Pediatric patients may demonstrate greater susceptibility to topical corticosteroid-induced hypothalmic-pituitary-adrenal (HPA) axis suppression and Cushing's syndrome than mature patients because of a larger skin surface area to body weight ratio.

Hypothalmic-pituitary-adrenal (HPA) axis suppression, Cushing's syndrome, and intracranial hypertension have been reported in children receiving topical corticosteroids. Manifestations of adrenal suppression in children include linear growth retardation, delayed weight gain, low plasma cortisol levels, and absence of response to ACTH stimulation. Manifestations of intracranial hypertension include bulging fontanelles, headaches, and bilateral papilledema.

Administration of topical corticosteroids to children should be limited to the least amount compatible with an effective therapeutic regimen. Chronic corticosteroid therapy may interfere with the growth and development of children.

ADVERSE REACTIONS

The following local adverse reactions are reported infrequently with topical corticosteroids. These reactions are listed in an approximate decreasing order of occurrence:

Burning | Hypertrichosis | Maceration of the skin
Itching | Acneiform eruptions | Secondary infection
Irritation | Hypopigmentation | Skin atrophy
Dryness | Perioral dermatitis | Striae
Folliculitis | Allergic contact dermatitis | Miliaria

The following adverse reactions have been reported with the topical use of neomycin:

Ototoxicity | Nephrotoxicity

OVERDOSAGE

Topically applied corticosteroids can be absorbed in sufficient amounts to produce systemic effects (see PRECAUTIONS).

DOSAGE AND ADMINISTRATION

NEO-SYNALAR® cream is generally applied to the affected area as a thin film from two to four times daily depending on the severity of the condition.

Since NEO-SYNALAR® cream is a water-washable vanishing cream, it is easily applied and leaves no traces.

HOW SUPPLIED

NEO-SYNALAR® [neomycin sulfate 0.5% (0.35% neomycin base), fluocinolone acetonide 0.025%] Cream is supplied in

60 g Tube – NDC 43538-940-60

STORAGE

Store at room temperature 15-25°C (59-77°F); avoid freezing and excessive heat above 40°C (104°F).

To report SUSPECTED ADVERSE REACTIONS, contact Medimetriks at 973-882-7512 or FDA at 1-800-FDA-1088 or www.fda/gov/medwatch.

Manufactured for:

MEDIMETRIKS
PHARMACEUTICALS, INC.

383 Route 46 West, Fairfield, NJ 07004-2402 USA • www.medimetriks.com
Manufactured by: Ferndale Laboratories, Inc., Ferndale, MI 48220

IP026-R3
Rev. 3/22

PRINCIPAL DISPLAY PANEL - 60 g Tube Carton

Rx Only

NDC 43538-940-60

NEO-SYNALAR®
[neomycin sulfate 0.5% (0.35% neomycin base),
fluocinolone acetonide 0.025%] Cream

60 g

For Topical Use Only
Not For Ophthalmic Use

MEDIMETRIKS
PHARMACEUTICALS, INC.